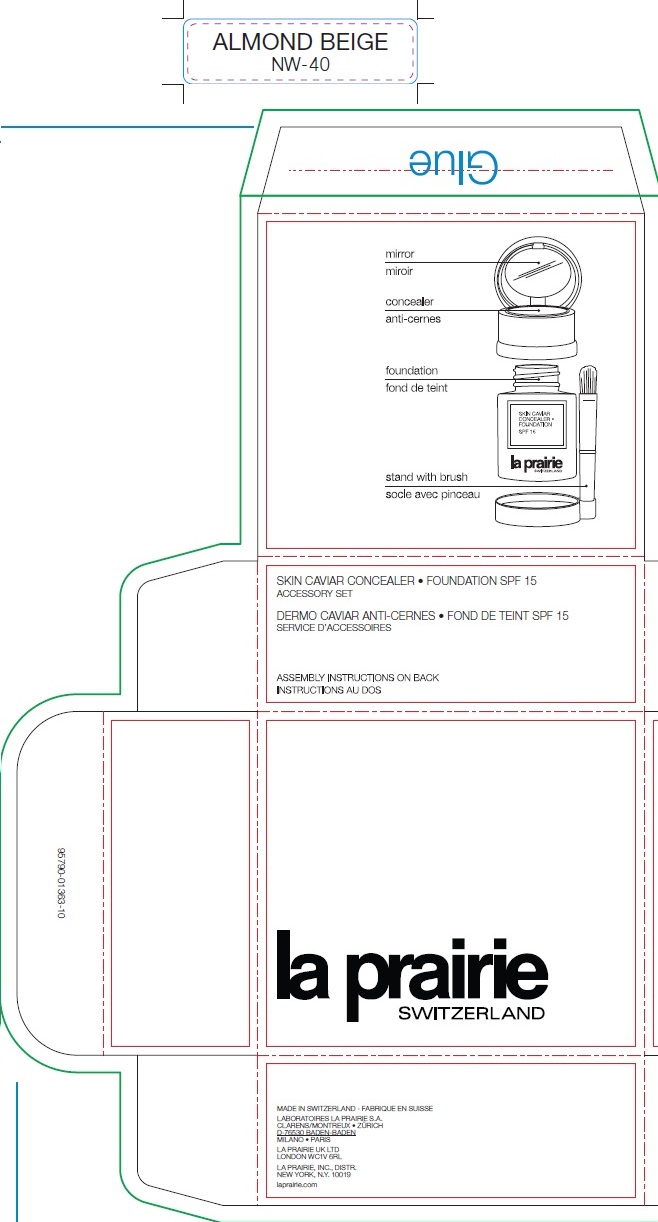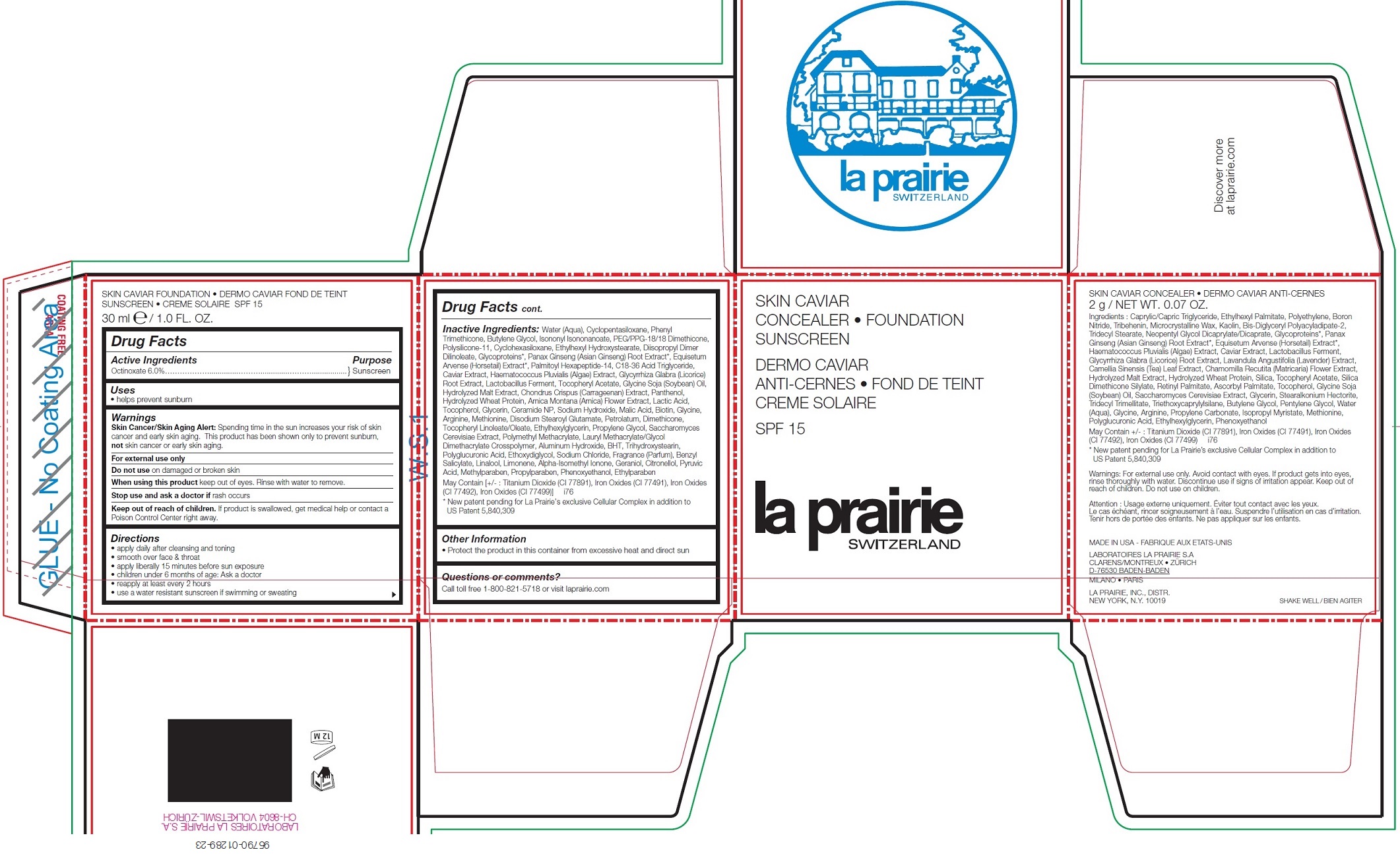 DRUG LABEL: La Prairie Concealer-Foundation Sunscreen SPF 15 - ALMOND BEIGE
NDC: 68026-816 | Form: KIT | Route: TOPICAL
Manufacturer: La Prairie, Inc.
Category: otc | Type: HUMAN OTC DRUG LABEL
Date: 20250221

ACTIVE INGREDIENTS: OCTINOXATE 60 mg/1 mL
INACTIVE INGREDIENTS: WATER; CYCLOMETHICONE 5; PHENYL TRIMETHICONE; BUTYLENE GLYCOL; ISONONYL ISONONANOATE; PEG/PPG-18/18 DIMETHICONE; DIMETHICONE/VINYL DIMETHICONE CROSSPOLYMER (SOFT PARTICLE); CYCLOMETHICONE 6; ETHYLHEXYL HYDROXYSTEARATE; DIISOPROPYL DILINOLEATE; ASIAN GINSENG; EQUISETUM ARVENSE BRANCH; C18-36 ACID TRIGLYCERIDE; CAVIAR, UNSPECIFIED; HAEMATOCOCCUS PLUVIALIS; GLYCYRRHIZA GLABRA; .ALPHA.-TOCOPHEROL ACETATE; SOYBEAN OIL; CHONDRUS CRISPUS CARRAGEENAN; PANTHENOL; ARNICA MONTANA FLOWER; LACTIC ACID; TOCOPHEROL; GLYCERIN; CERAMIDE NP; SODIUM HYDROXIDE; MALIC ACID; BIOTIN; GLYCINE; ARGININE; METHIONINE; DISODIUM STEAROYL GLUTAMATE; PETROLATUM; DIMETHICONE; OLEIC ACID; ETHYLHEXYLGLYCERIN; PROPYLENE GLYCOL; SACCHAROMYCES CEREVISIAE; LAURYL METHACRYLATE/GLYCOL DIMETHACRYLATE CROSSPOLYMER; ALUMINUM HYDROXIDE; BUTYLATED HYDROXYTOLUENE; TRIHYDROXYSTEARIN; DIETHYLENE GLYCOL MONOETHYL ETHER; SODIUM CHLORIDE; BENZYL SALICYLATE; LIMONENE, (+)-; ISOMETHYL-.ALPHA.-IONONE; GERANIOL; .BETA.-CITRONELLOL, (R)-; PYRUVIC ACID; METHYLPARABEN; PROPYLPARABEN; PHENOXYETHANOL; ETHYLPARABEN

La Prairie Concealer-Foundation Sunscreen SPF 15 - ALMOND BEIGE

Active Ingredients

Octinoxate 6.0%

Purpose

Sunscreen

Uses

• helps prevent sunburn

Warnings

Skin Cancer/Skin Aging Alert: Spending time in the sun increases your risk of skin cancer and early skin aging. This product has been shown only to prevent sunburn, not skin cancer or early skin aging.

For external use only

Do not use

on damaged or broken skin

When using this product

keep out of eyes. Rinse with water to remove.

Stop use and ask a doctor if

rash occurs

Keep out of reach of children.

If product is swallowed, get medical help or contact a Poison Control Center right away.

Directions

• apply daily after cleansing and toning
• smooth over face & throat
• apply liberally 15 minutes before sun exposure
• children under 6 months of age: Ask a doctor
• reapply at least every 2 hours
• use a water resistant sunscreen if swimming or sweating

Inactive Ingredients:

Water (Aqua), Cyclopentasiloxane, Phenyl Trimethicone, Butylene Glycol, Isononyl Isononanoate, PEG/PPG-18/18 Dimethicone, Polysilicone-11, Cyclohexasiloxane, Ethylhexyl Hydroxystearate, Diisopropyl Dimer Dilinoleate, Glycoproteins*, Panax Ginseng (Asian Ginseng) Root Extract*, Equisetum Arvense (Horsetail) Extract*, Palmitoyl Hexapeptide-14, C18-36 Acid Triglyceride, Caviar Extract, Haematococcus Pluvialis (Algae) Extract, Glycyrrhiza Glabra (Licorice) Root Extract, Lactobacillus Ferment, Tocopheryl Acetate, Glycine Soja (Soybean) Oil, Hydrolyzed Malt Extract, Chondrus Crispus (Carrageenan) Extract, Panthenol, Hydrolyzed Wheat Protein, Arnica Montana (Arnica) Flower Extract, Lactic Acid, Tocopherol, Glycerin, Ceramide NP, Sodium Hydroxide, Malic Acid, Biotin, Glycine, Arginine, Methionine, Disodium Stearoyl Glutamate, Petrolatum, Dimethicone, Tocopheryl Linoleate/Oleate, Ethylhexylglycerin, Propylene Glycol, Saccharomyces Cerevisiae Extract, Polymethyl Methacrylate, Lauryl Methacrylate/Glycol Dimethacrylate Crosspolymer, Aluminum Hydroxide, BHT, Trihydroxystearin, Polyglucuronic Acid, Ethoxydiglycol, Sodium Chloride, Fragrance (Parfum), Benzyl Salicylate, Linalool, Limonene, Alpha-Isomethyl Ionone, Geraniol, Citronellol, Pyruvic Acid, Methylparaben, Propylparaben, Phenoxyethanol, Ethylparaben May Contain [+/- : Titanium Dioxide (CI 77891), Iron Oxides (CI 77491), Iron Oxides (CI 77492), Iron Oxides (CI 77499)] i76
* New patent pending for La Prairie’s exclusive Cellular Complex in addition to US Patent 5,840,309

Other Information

• Protect the product in this container from excessive heat and direct sun

Questions or comments?

Call toll free 1-800-821-5718 or visit laprairie.com